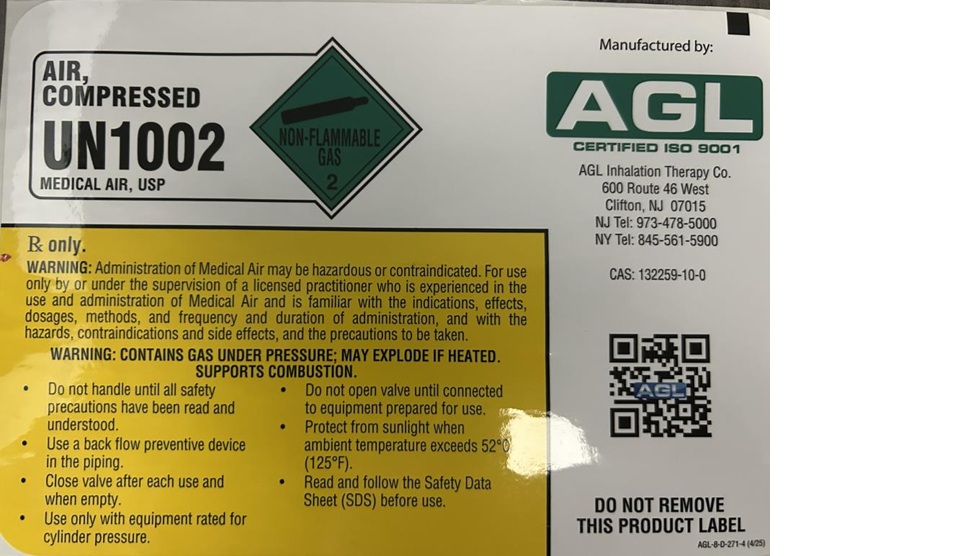 DRUG LABEL: Air
NDC: 17575-300 | Form: GAS
Manufacturer: AGL Welding Supply Co., Inc.
Category: prescription | Type: HUMAN PRESCRIPTION DRUG LABEL
Date: 20251022

ACTIVE INGREDIENTS: OXYGEN 210 mL/1 L

air

PACKAGE LABEL

AIR, COMPRESSED

UN1002

MEDICAL AIR, USP

Rx only.

WARNING: Administration of Medical Air may be hazardous or contraindicated. For use only by or under the supervision of a licensed practitioner who is experienced in the use and administration of Medical Air and is familiar with the indications, effects, dosages, methods, and frequency and duration of administration, and with the hazards, contraindications and side effects, and the precautions to be taken.

WARNING: CONTAINS GAS UNDER PRESSURE; MAY EXPLODE IF HEATED.

SUPPORTS COMBUSTION.

Do not handle until all safety precautions have been read and understood.

Use a back flow preventive device in the piping.

Close valve after each use and when empty.

Use only with equipment rated for cylinder pressure.

Do not open valve until connected to equipment prepared for use.

Protect from sunlight when ambient temperature exceeds 52 C (125 F).

Read and follow the Safety Data Sheet (SDS) before use.

Manufactured by:

AGL

CERTIFIED ISO 9001

AGL Inhalation Therapy Co.

600 Route 46 West

Clifton, NJ 07015

NJ Tel: 973-478-5000

NY Tel: 845-561-5900

CAS: 132259-10-0

DO NOT REMOVE THIS PRODUCT LABEL